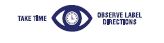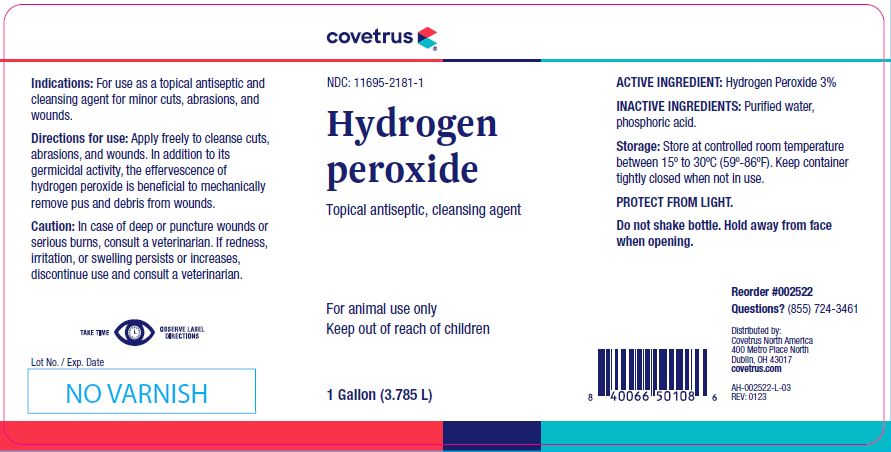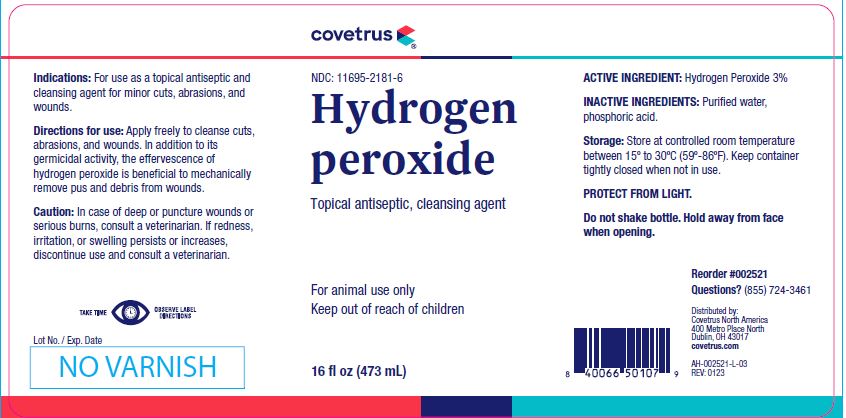 DRUG LABEL: Hydrogen Peroxide
NDC: 11695-2181 | Form: SOLUTION
Manufacturer: Butler Animal health Supply, LLC dba Covetrus North America
Category: animal | Type: OTC ANIMAL DRUG LABEL
Date: 20230605

ACTIVE INGREDIENTS: HYDROGEN PEROXIDE 59.2 g/1 L

Hydrogen
peroxide

STATEMENT OF IDENTITY

Topical antiseptic, cleansing agent

KEEP OUT OF REACH OF CHILDREN

For animal use only
Keep out of reach of children

HOW SUPPLIED

16 fl oz (473 mL) Reorder #002521

1 Gallon (3.785 L) Reorder #002522

Indications:

For use as a topical antiseptic and cleansing agent for minor cuts, abrasions, and wounds.

Directions for use:

Apply freely to cleanse cuts, abrasions, and wounds. In addition to its germicidal activity, the effervescence of hydrogen peroxide is beneficial to mechanically remove pus and debris from wounds.

Caution:

In case of deep or puncture wounds or serious burns, consult a veterinarian. If redness, irritation, or swelling persists or increases, discontinue use and consult a veterinarian.

ACTIVE INGREDIENT:

Hydrogen Peroxide 3%

INACTIVE INGREDIENTS:

Purified water, phosphoric acid.

Storage:

Store at controlled room temperature between 15º to 30ºC (59º-86ºF). Keep container tightly closed when not in use.

PROTECT FROM LIGHT.

Do not shake bottle. Hold away from face when opening.

INFORMATION FOR OWNERS/CAREGIVERS

Questions? (855) 724-3461
Distributed by:
Covetrus North America
400 Metro Place North
Dublin, OH 43017
covetrus.com

AH-002521-L-03
REV: 0123

AH-002522-L-03
REV: 0123